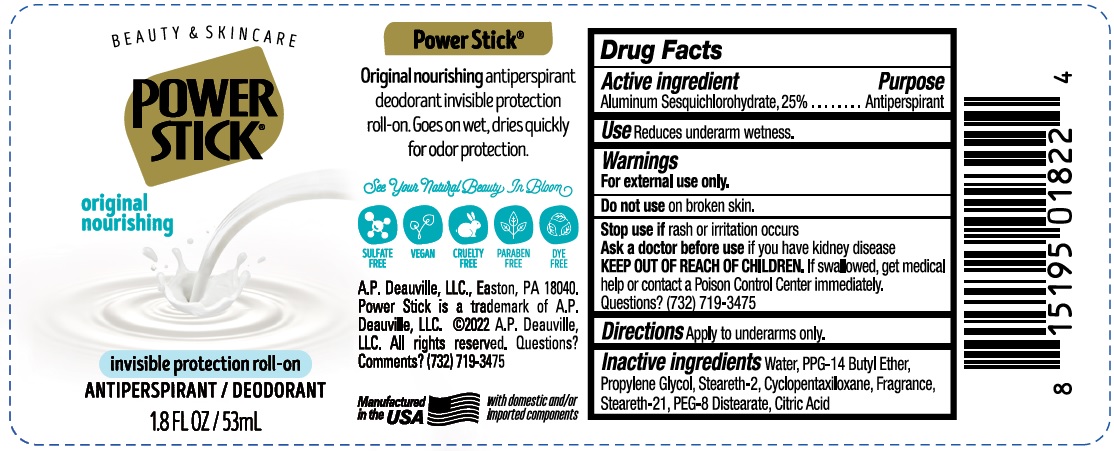 DRUG LABEL: Power Stick Original Nourishing Invisible Protection Roll- On Antiperspirant Deodorant
NDC: 42913-040 | Form: STICK
Manufacturer: A.P. Deauville, LLC
Category: otc | Type: HUMAN OTC DRUG LABEL
Date: 20240715

ACTIVE INGREDIENTS: ALUMINUM SESQUICHLOROHYDRATE 250 mg/1 mL
INACTIVE INGREDIENTS: WATER; PPG-14 BUTYL ETHER; PROPYLENE GLYCOL; STEARETH-2; CYCLOMETHICONE 5; STEARETH-21; PEG-8 DISTEARATE; CITRIC ACID MONOHYDRATE

Power Stick Original Nourishing Invisible Protection Roll- On Antiperspirant Deodorant

Active ingredient

Aluminum Sesquichlorohydrate, 25%

Purpose

Antiperspirant

Use

Reduces underarm wetness.

Warnings

For external ues only.

Do not use

on broken skin.

Stop use if

rash or irritation occurs

Ask a doctor before use

if you have kidney disease

KEEP OUT OF REACH OF CHILDREN.

If swallowed, get medical help or contact a Poison Control Center immediately.

Questions?

(732) 719-3475

Directions

Apply to underams only.

Inactive ingredients

Water, PPG-14 Butyl Ether, Propylene Glycol, Steareth-2, Cyclopentasiloxane, Fragrance, Steareth-21, PEG-8 Distearate, Citric Acid